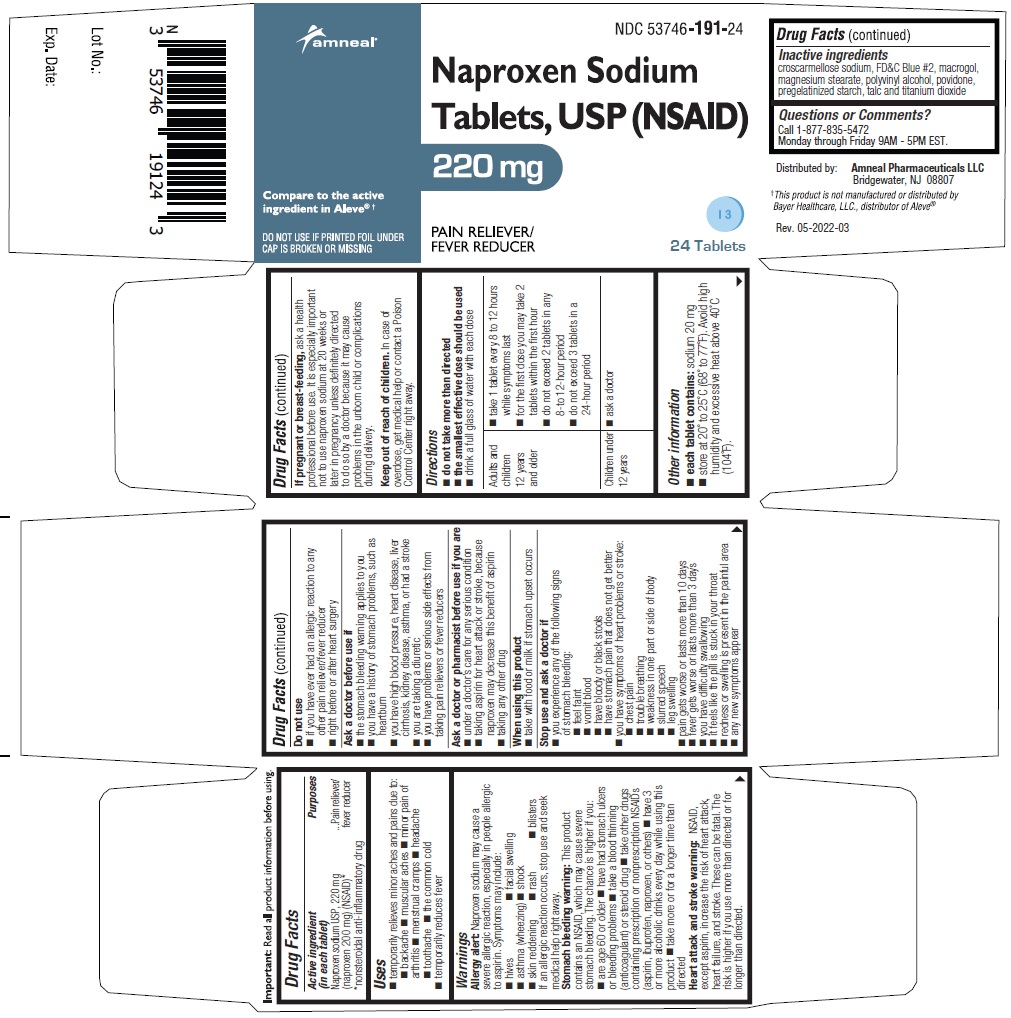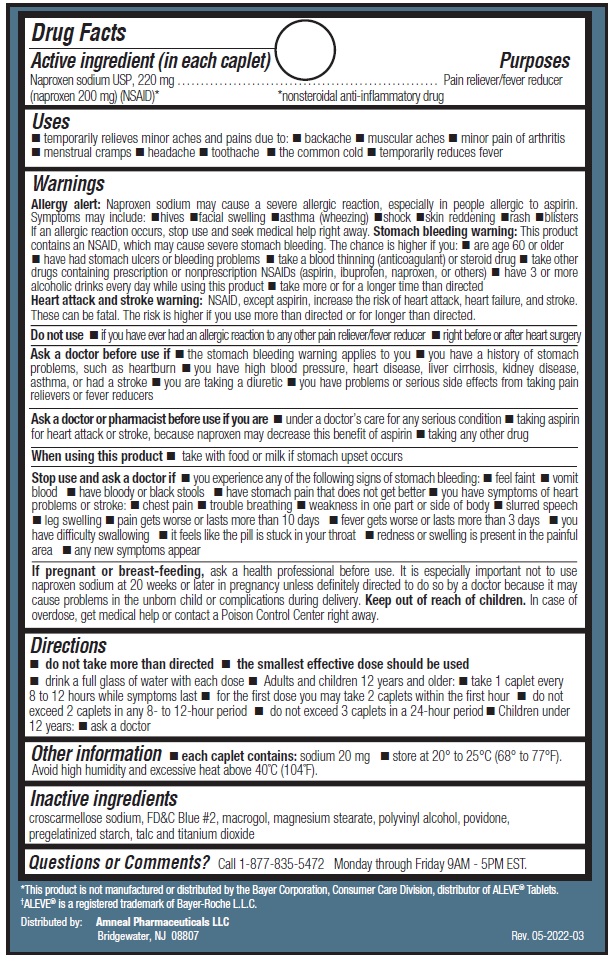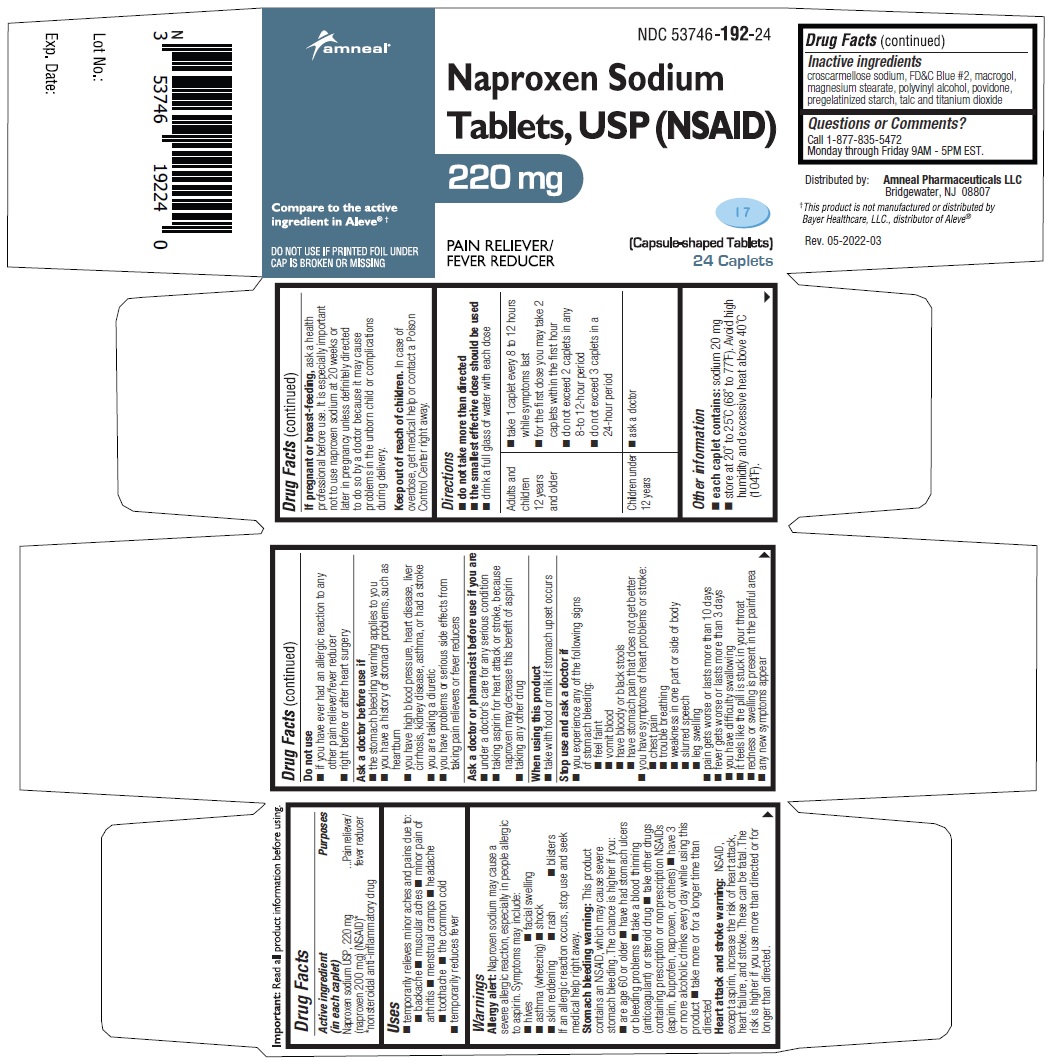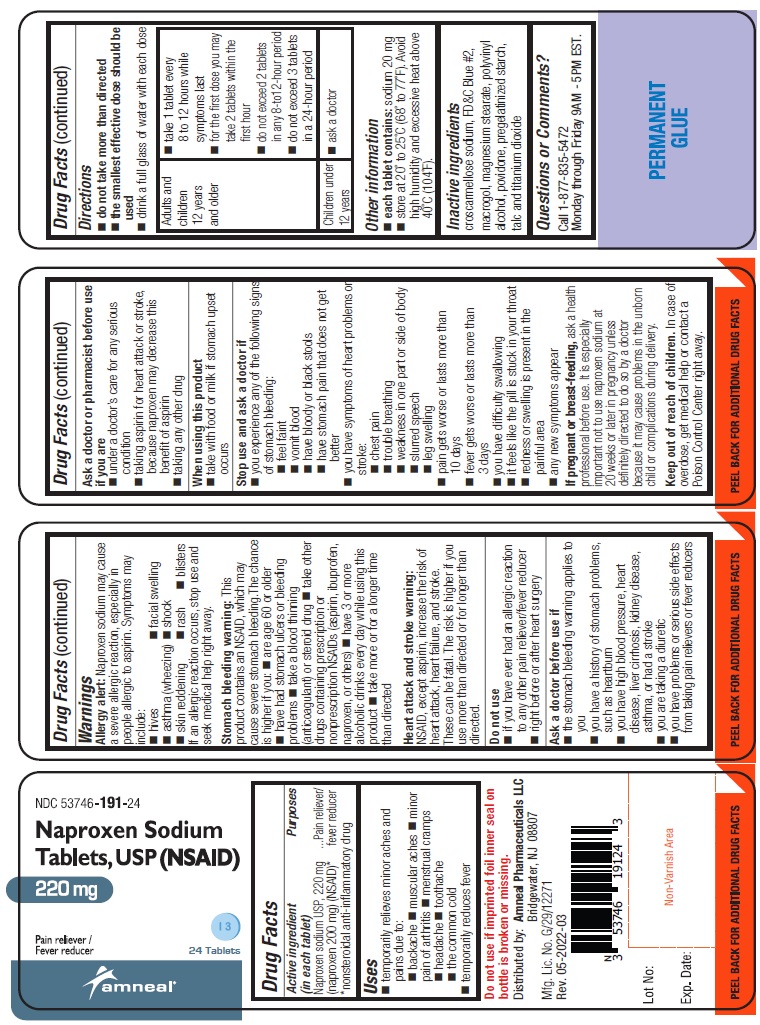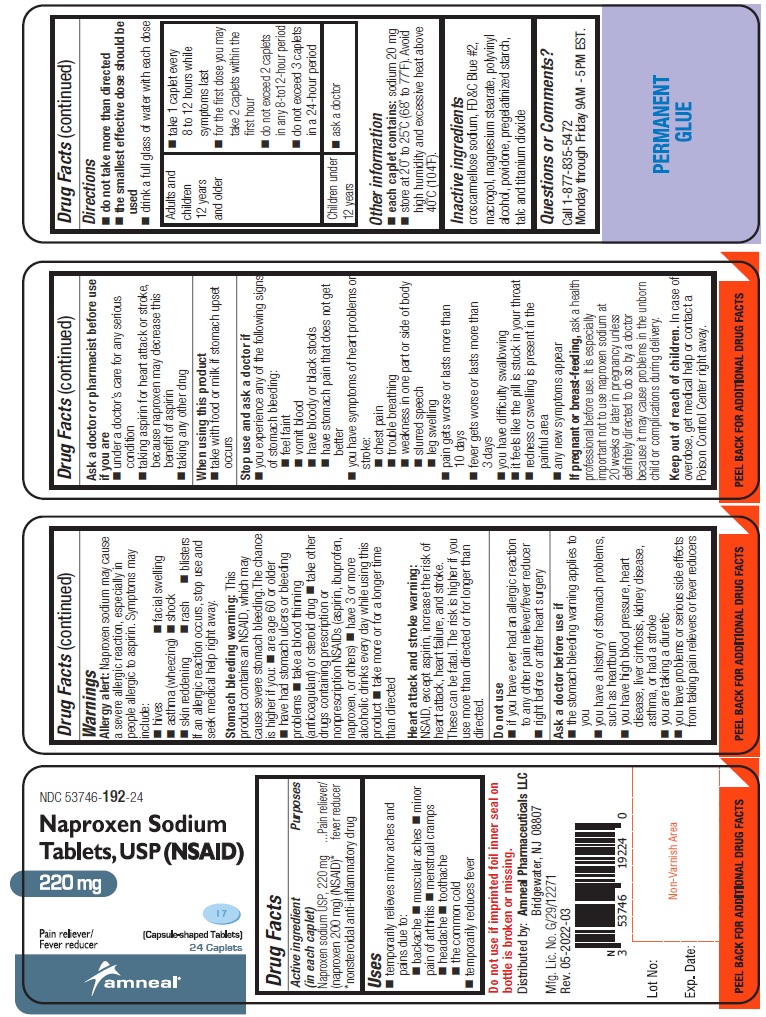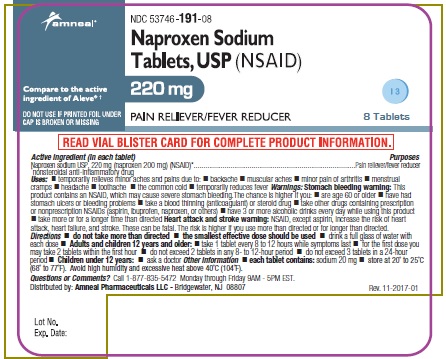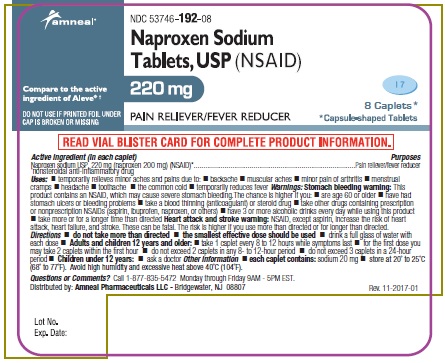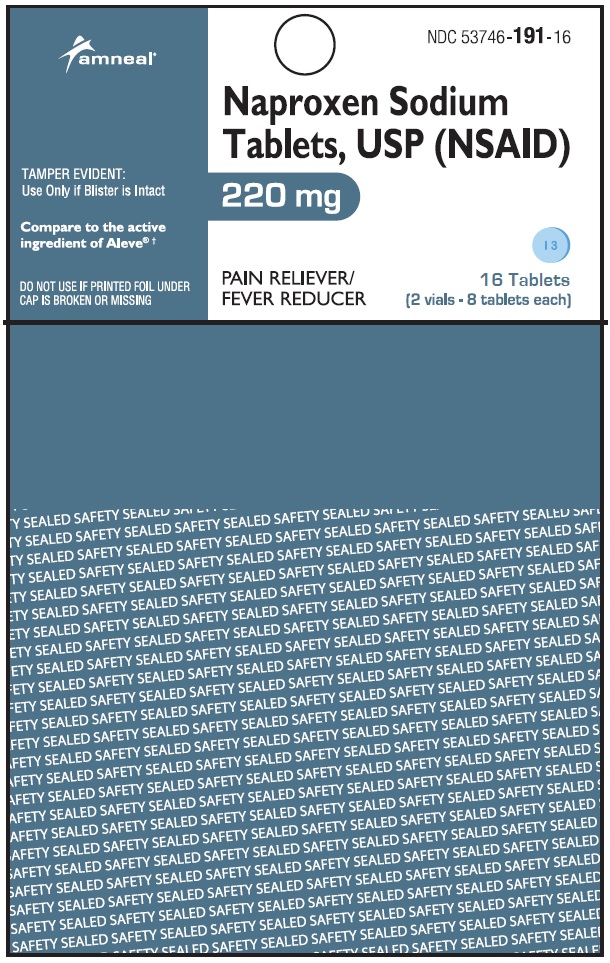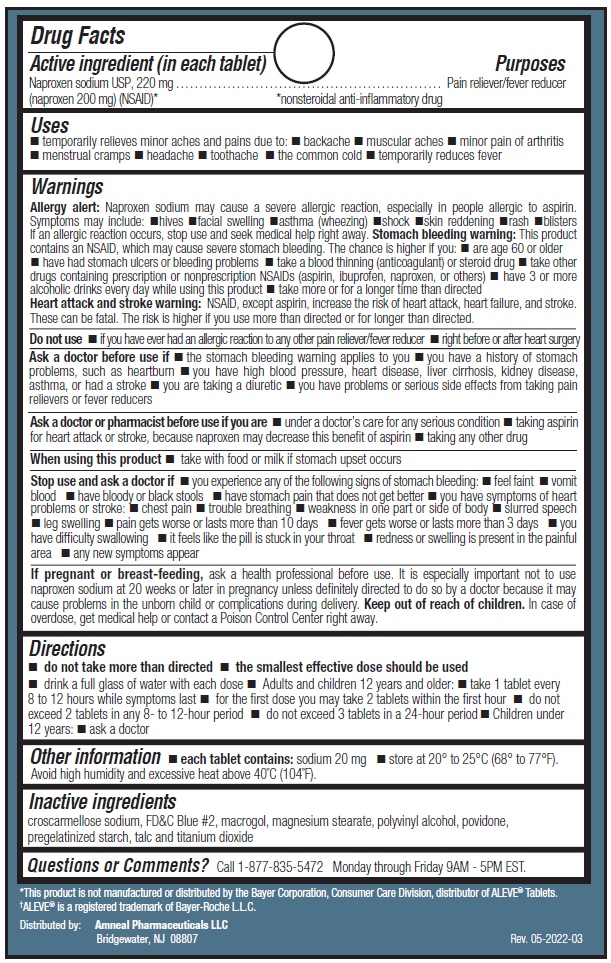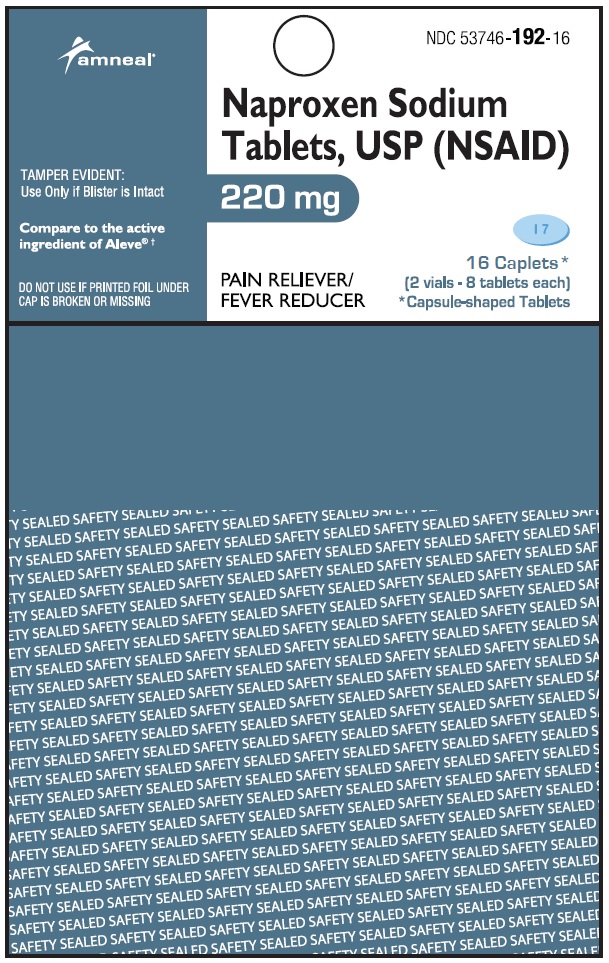 DRUG LABEL: Naproxen Sodium (NSAID)
NDC: 53746-191 | Form: TABLET
Manufacturer: Amneal Pharmaceuticals of New York LLC
Category: otc | Type: HUMAN OTC DRUG LABEL
Date: 20231231

ACTIVE INGREDIENTS: NAPROXEN SODIUM 220 mg/1 1
INACTIVE INGREDIENTS: FD&C BLUE NO. 2; CROSCARMELLOSE SODIUM; POLYETHYLENE GLYCOL, UNSPECIFIED; MAGNESIUM STEARATE; POLYVINYL ALCOHOL, UNSPECIFIED; POVIDONE; STARCH, CORN; TALC; TITANIUM DIOXIDE

Naproxen Sodium Tablets, USP
Pain Reliever/ Fever Reducer (NSAID)
220 mg

Compared to the active ingredient of Aleve® †

Drug Facts

ACTIVE INGREDIENT

(in each tablet)

Naproxen sodium USP, 220 mg

(naproxen 200 mg) (NSAID)*

*nonsteroidal anti-inflammatory drug

PURPOSE

Pain reliever/fever reducer

INDICATION AND USAGE

Uses

- temporarily relieves minor aches and pains due to:
- backache
- muscular aches
- minor pain of arthritis
- menstrual cramps
- headache
- toothache
- the common cold
- temporarily reduces fever

WARNINGS

Allergy alert: Naproxen sodium may cause a severe allergic reaction, especially in people allergic to aspirin. Symptoms may include:

- hives
- facial swelling
- asthma (wheezing)
- shock
- skin reddening
- rash
- blisters

If an allergic reaction occurs, stop use and seek medical help right away.

Stomach bleeding warning: This product contains an NSAID, which may cause severe stomach bleeding. The chance is higher if you:

- are age 60 or older
- have had stomach ulcers or bleeding problems
- take a blood thinning (anticoagulant) or steroid drug
- take other drugs containing prescription or nonprescription NSAIDs (aspirin, ibuprofen, naproxen, or others)
- have 3 or more alcoholic drinks every day while using this product
- take more or for a longer time than directed

Heart attack and stroke warning: NSAID, except aspirin, increase the risk of heart attack, heart failure, and stroke. These can be fatal. The risk is higher if you use more than directed or for longer than directed.

DO NOT USE

- if you have ever had an allergic reaction to any other pain reliever/fever reducer
- right before or after heart surgery

ASK DOCTOR/PHARMACIST

Ask a doctor before use if

- the stomach bleeding warning applies to you
- you have a history of stomach problems, such as heartburn
- you have high blood pressure, heart disease, liver cirrhosis, kidney disease, asthma, or had a stroke
- you are taking a diuretic
- you have problems or serious side effects from taking pain relievers or fever reducers

Ask a doctor or pharmacist before use if you are

- under a doctor’s care for any serious condition
- taking aspirin for heart attack or stroke, because naproxen may decrease this benefit of aspirin
- taking any other drug

WHEN USING

When using this product

- take with food or milk if stomach upset occurs

STOP USE

Stop use and ask a doctor if

- you experience any of the following signs of stomach bleeding:
- feel faint
- vomit blood
- have bloody or black stools
- have stomach pain that does not get better

- you have symptoms of heart problems or stroke:
- chest pain
- trouble breathing
- weakness in one part or side of body
- slurred speech
- leg swelling
- pain gets worse or lasts more than 10 days
- fever gets worse or lasts more than 3 days
- you have difficulty swallowing
- it feels like the pill is stuck in your throat
- redness or swelling is present in the painful area
- any new symptoms appear

PREGNANCY OR BREAST FEEDING

If pregnant or breast-feeding, ask a health professional before use. It is especially important not to use naproxen sodium at 20 weeks or later in pregnancy unless definitely directed to do so by a doctor because it may cause problems in the unborn child or complications during delivery.

Keep out of reach of children. In case of overdose, get medical help or contact a Poison Control Center right away.

Directions

- do not take more than directed
- the smallest effective dose should be used
- drink a full glass of water with each dose

Adults and children 12 years and older | - take 1 tablet every 8 to 12 hours while symptoms last - for the first dose you may take 2 tablets within the first hour - do not exceed 2 tablets in any 8- to 12-hour period - do not exceed 3 tablets in a 24-hour period
Children under 12 years | - ask a doctor

Other information

- each tablet contains: sodium 20 mg
- store at 20 to 25°C (68 to 77°F). Avoid high humidity and excessive heat above 40°C (104°F).

INACTIVE INGREDIENT

croscarmellose sodium, FD&C Blue #2, macrogol, magnesium stearate, polyvinyl alcohol, povidone, pregelatinized starch, talc and titanium dioxide

Questions or Comments?

Call 1-877-835-5472

Monday through Friday 9 AM – 5 PM EST.

Distributed by:

Amneal Pharmaceuticals LLC

Bridgewater, NJ 08807

† This product is not manufactured or distributed by Bayer Healthcare, LLC., distributor of Aleve®

Rev. 05-2022-03

PACKAGE LABEL.PRINCIPAL DISPLAY PANEL

NDC 53746-191-24

Naproxen Sodium Tablets USP (NSAID), 220 mg

24 Tablets

Amneal Pharmaceuticals LLC
NDC 53746-192-24

Naproxen Sodium Tablets USP (NSAID), 220 mg

24 Caplets

Amneal Pharmaceuticals LLC

NDC 53746-191-24

Naproxen Sodium Tablets USP (NSAID), 220 mg

24 Tablets

Amneal Pharmaceuticals LLC

NDC 53746-192-24

Naproxen Sodium Tablets USP (NSAID), 220 mg

24 Caplets

Amneal Pharmaceuticals LLC

Purse Pack

NDC 53746-191-08

Naproxen Sodium Tablets USP (NSAID), 220 mg

8 Tablets

Amneal Pharmaceuticals LLC

Purse Pack

NDC 53746-192-08

Naproxen Sodium Tablets USP (NSAID), 220 mg

8 Caplets

Amneal Pharmaceuticals LLC

Purse Pack

NDC 53746-191-16

Naproxen Sodium Tablets USP (NSAID), 220 mg

16 Tablets

Amneal Pharmaceuticals LLC

Purse Pack

NDC 53746-192-16

Naproxen Sodium Tablets USP (NSAID), 220 mg

16 Caplets

Amneal Pharmaceuticals LLC